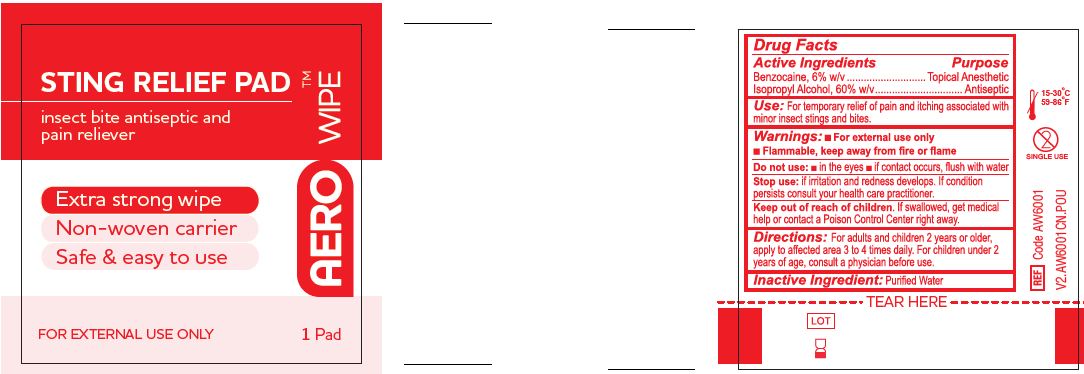 DRUG LABEL: AeroWipe
NDC: 55305-125 | Form: SWAB
Manufacturer: Aero Healthcare US LLC
Category: otc | Type: HUMAN OTC DRUG LABEL
Date: 20250829

ACTIVE INGREDIENTS: BENZOCAINE 60 mg/1 mL; ISOPROPYL ALCOHOL 600 mg/1 mL
INACTIVE INGREDIENTS: WATER

AeroWipe Sting Relief Pad

Active Ingredients

Benzocaine 6% w/v

Isopropyl alcohol 60% w/v

Purpose

Topical anesthetic

Antiseptic

Use

For temporary relief of pain and itching associated with minor insect stings and bites

Warnings

For external use only.

Flammable, keep away from fire or flame.

Do not use:

- in the eyes. If contact occurs, rinse thoroughly with water.

Stop use

- if irritation and redness develops. If condition persists consult your health care practitioner.

Keep out of reach of children.

If swallowed, get medical help or contact a Poison Control Center right away.

Directions

For adults and children 2 years or older, apply to affected area 3 to 4 times daily. For children under 2 years of age, consult a physician before use.

Inactive Ingredient

Purified Water

PACKAGE LABEL

AEROWIPE

Sting Relief Pad

insect bite antiseptic and pain reliever

Extra Strong Wipe

Non-Woven Carrier

Safe & easy to use

FOR EXTERNAL USE ONLY

1 Pad